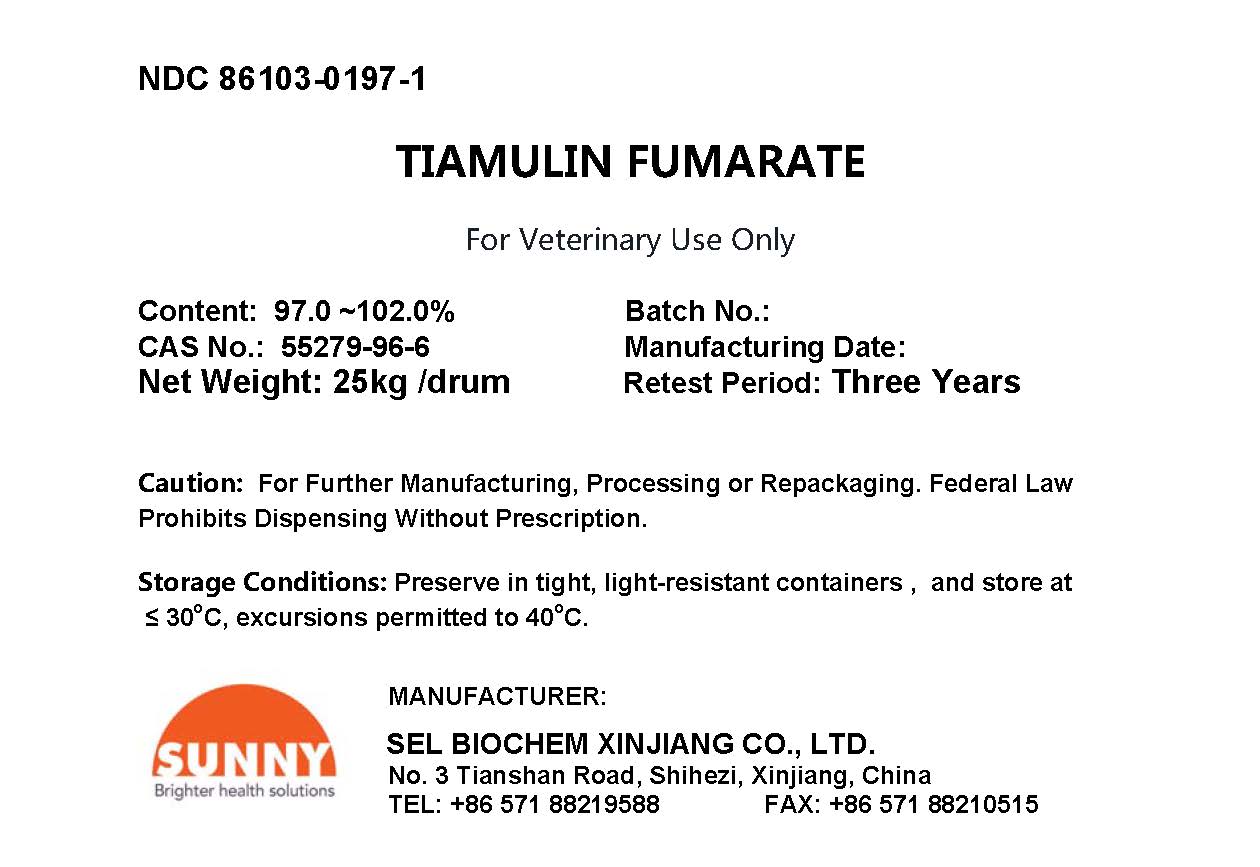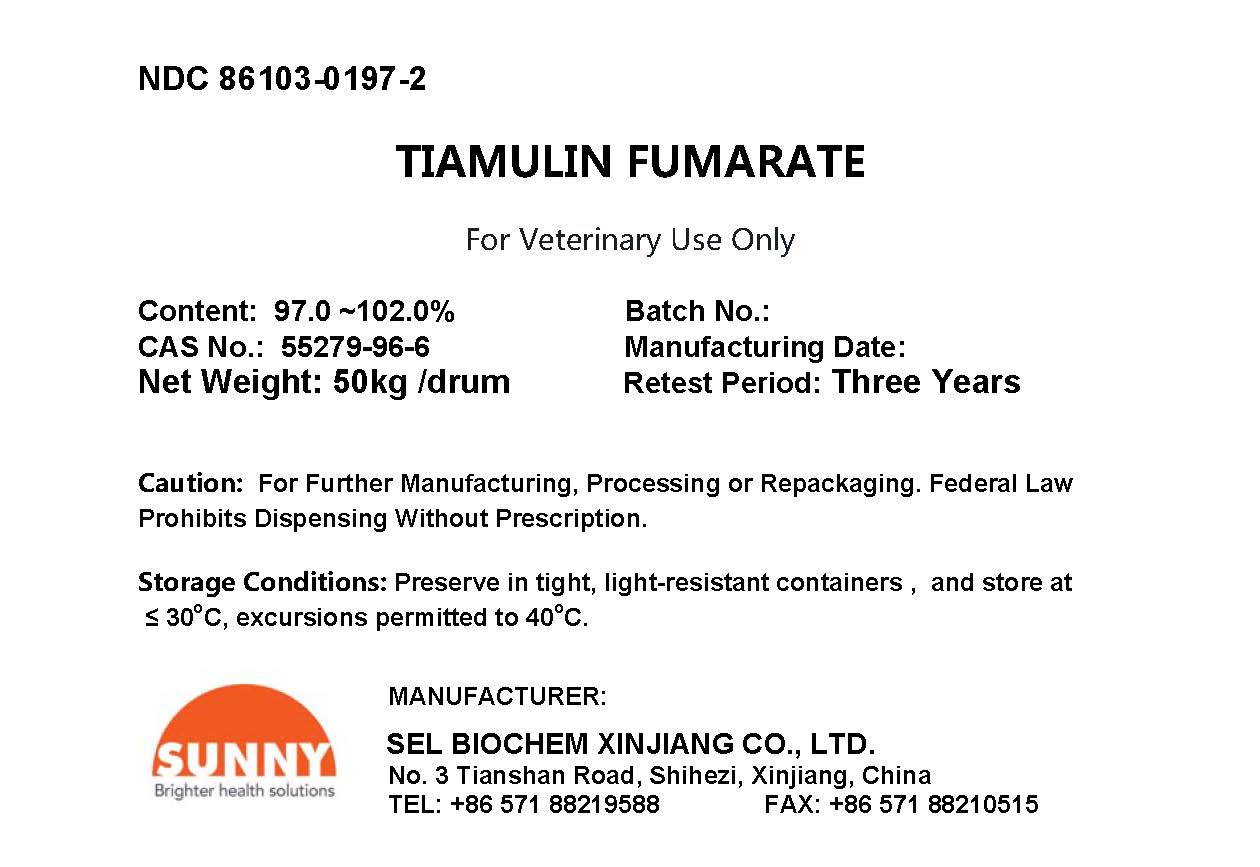 DRUG LABEL: Tiamulin Fumarate
NDC: 86103-0197 | Form: POWDER
Manufacturer: SEL Biochem Xinjiang Co., Ltd.
Category: other | Type: BULK INGREDIENT - ANIMAL DRUG
Date: 20241104

ACTIVE INGREDIENTS: TIAMULIN FUMARATE 24.25 kg/25 kg

Tiamulin Fumarate

PACKAGE LABEL

DC 86103-0197-1
TIAMULIN FUMARATE
For Veterinary Use Only
Content: 97.0 ~102.0% Batch No.:
CAS No.: 55279-96-6 Manufacturing Date:
Net Weight: 25kg/drum Retest Period: Three Years
Caution: For Further Manufacturing, Processing or Repackaging. Federal Law Prohibits Dispensing Without Prescription.
Storage Conditions: Preserve in tight, light-resistant containers, and store at ≤30oC, excursions permitted to 40oC.
MANUFACTURER:
SEL BIOCHEM XINJIANG CO., LTD.
No. 3 Tianshan Road, Shihezi, Xinjiang, China
TEL: +86 571 88219588 FAX: +86 571 88210515

PACKAGE LABEL

NDC 86103-0197-2
TIAMULIN FUMARATE
For Veterinary Use Only
Content: 97.0 ~102.0% Batch No.:
CAS No.: 55279-96-6 Manufacturing Date:
Net Weight: 50kg/drum Retest Period: Three Years
Caution: For Further Manufacturing, Processing or Repackaging. Federal Law Prohibits Dispensing Without Prescription.
Storage Conditions: Preserve in tight, light-resistant containers, and store at ≤30oC, excursions permitted to 40oC.
MANUFACTURER:
SEL BIOCHEM XINJIANG CO., LTD.
No. 3 Tianshan Road, Shihezi, Xinjiang, China
TEL: +86 571 88219588 FAX: +86 571 88210515